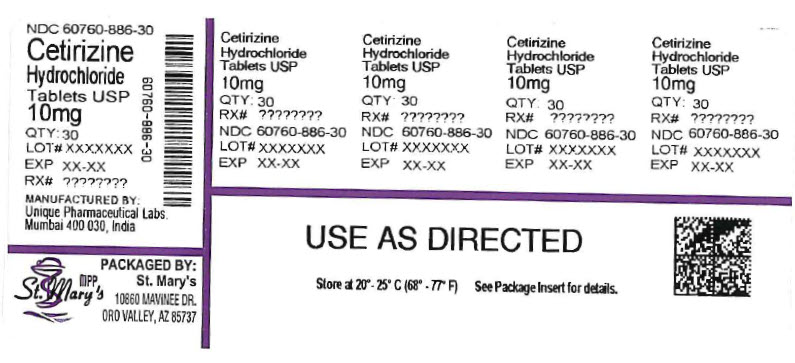 DRUG LABEL: Cetirizine Hydrochloride
NDC: 60760-886 | Form: TABLET
Manufacturer: ST. MARY'S MEDICAL PARK PHARMACY
Category: otc | Type: HUMAN OTC DRUG LABEL
Date: 20251205

ACTIVE INGREDIENTS: CETIRIZINE HYDROCHLORIDE 10 mg/1 1
INACTIVE INGREDIENTS: HYPROMELLOSES; LACTOSE; MAGNESIUM STEARATE; STARCH, CORN; POLYETHYLENE GLYCOL; POVIDONE; TITANIUM DIOXIDE

Cetirizine Hydrochloride Tablets USP, 10 mg, Allergy

ACTIVE INGREDIENTS

Active Ingredients (in each tablet) Purpose

Cetirizine HCl USP 10 mg................................................................Antihistimine

PURPOSE

Antihistamine

USES

Temporarily relieves these symptoms due to hay fever or other upper respiratory allergies

- runny nose
- sneezing
- itchy, watery eyes
- itching of the nose or throat

WARNINGS

Do Not Use if you have ever had an allergic reaction to this product or any of its ingredients or to an antihistamine containing hydroxyzine.

ASK DOCTOR

Ask a doctor before use if you have liver or kidney disease. Your doctor should determine if you need a different dose.

ASK DOCTOR/PHARMACIST

Ask a doctor or pharmacist before use if you are taking tranquilizers or sedatives.

WHEN USING THIS PRODUCT

- drowsines may occur
- avoid alcoholic drinks
- alcohol, sedatives, and tranquilizers may increase drowsiness
- be careful when driving a motor vehicle or operating machinary.

STOP USE

Stop use and ask a doctor if an allergic reaction tothis product occurs. Seek medical help right away.

IF PREGNANT OR BREAST FEEDING:

- if breast-feeding: not recommended
- if pregnant: ask a health professional before use.

KEEP OUT OF REACH OF CHILDREN

In case of overdose, get medical help or contact Poison Control Center right away.

DIRECTIONS

Adults and children 6 years and over | one 10 mg tablet once daily, do not take more than one 10 mg tablet in 24 hours. A 5 mg product may be appropriate for less severe symptoms.
Adults 65 years and over | Ask a doctor
Children under 6 years of age | Ask a doctor
Consumers with liver or kidney disease | Ask a doctor

OTHER INFORMATION

store at 20° to 25°C (68° to 77°F)

[See USP Controlled Room Temperature]

INACTIVE INGREDIENTS

Hypromellose, lactose, magnesium stearate, maize starch, polyethylene glycol, povidone, titanium dioxide.

QUESTIONS?

Call 1-844-874-7464

Manufactured by:

Unique Pharmaceutical Labs.

(A Div. of J. B. Chemicals & Pharmaceuticals Ltd.),
Mumbai 400 030, India

Distributed by:

Rising Pharma holdings, Inc.
East Brunswick, NJ 08816

M. L. G/1430 Jul. 2020

126406